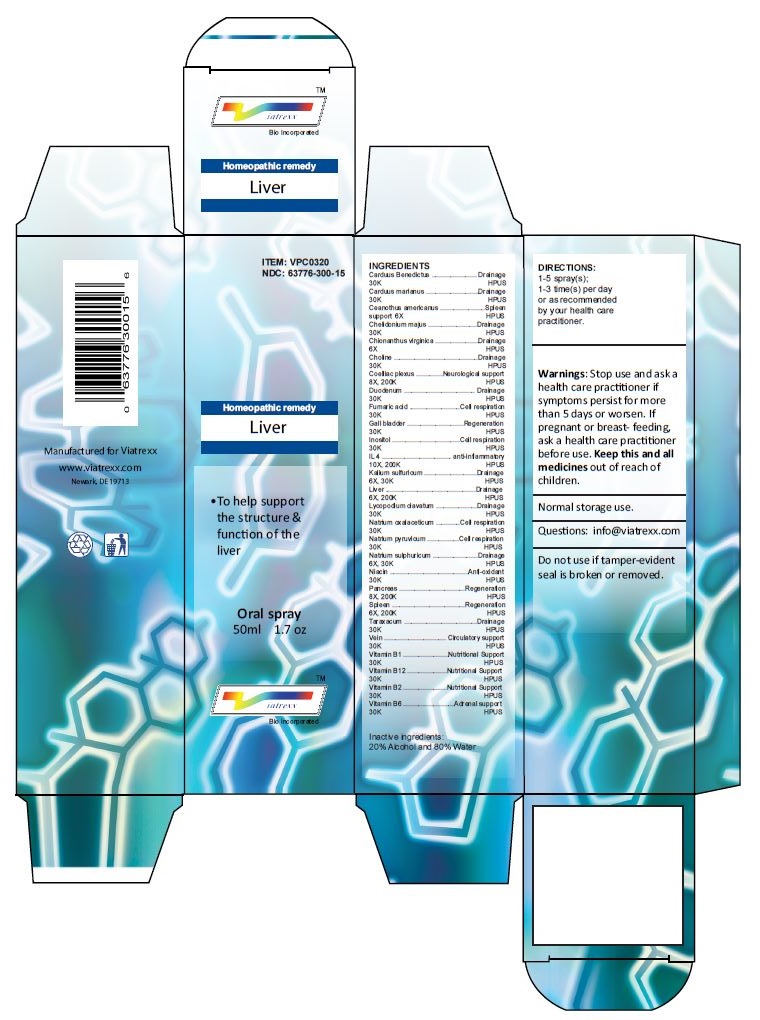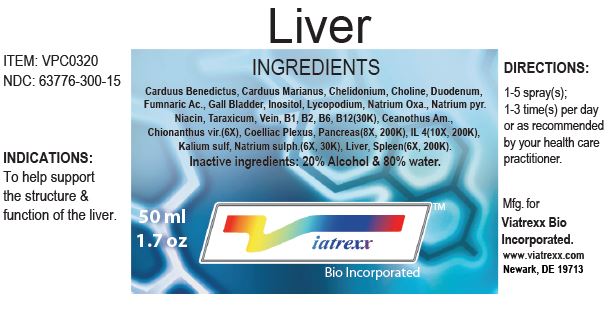 DRUG LABEL: Liver
NDC: 63776-300 | Form: SPRAY
Manufacturer: VIATREXX BIO INCORPORATED
Category: homeopathic | Type: HUMAN OTC DRUG LABEL
Date: 20221130

ACTIVE INGREDIENTS: TARAXACUM OFFICINALE 30 [kp_C]/1 mL; BOS TAURUS VEIN 30 [kp_C]/1 mL; SUS SCROFA VEIN 30 [kp_C]/1 mL; THIAMINE 30 [kp_C]/1 mL; CYANOCOBALAMIN 30 [kp_C]/1 mL; RIBOFLAVIN 30 [kp_C]/1 mL; PYRIDOXINE 30 [kp_C]/1 mL; CENTAUREA BENEDICTA 30 [kp_C]/1 mL; SILYBUM MARIANUM SEED 30 [kp_C]/1 mL; CEANOTHUS AMERICANUS LEAF 6 [hp_X]/1 mL; CHELIDONIUM MAJUS 30 [kp_C]/1 mL; CHIONANTHUS VIRGINICUS BARK 6 [hp_X]/1 mL; CHOLINE 30 [kp_C]/1 mL; BOS TAURUS SOLAR PLEXUS 200 [kp_C]/1 mL; SUS SCROFA SOLAR PLEXUS 200 [kp_C]/1 mL; BOS TAURUS DUODENUM 30 [kp_C]/1 mL; SUS SCROFA DUODENUM 30 [kp_C]/1 mL; FUMARIC ACID 30 [kp_C]/1 mL; BOS TAURUS GALLBLADDER 30 [kp_C]/1 mL; SUS SCROFA GALLBLADDER 30 [kp_C]/1 mL; INOSITOL 30 [kp_C]/1 mL; BINETRAKIN 200 [kp_C]/1 mL; POTASSIUM SULFATE 30 [kp_C]/1 mL; BEEF LIVER 200 [kp_C]/1 mL; PORK LIVER 200 [kp_C]/1 mL; LYCOPODIUM CLAVATUM SPORE 30 [kp_C]/1 mL; SODIUM DIETHYL OXALACETATE 30 [kp_C]/1 mL; SODIUM PYRUVATE 30 [kp_C]/1 mL; SODIUM SULFATE 30 [kp_C]/1 mL; NIACIN 30 [kp_C]/1 mL; BOS TAURUS PANCREAS 200 [kp_C]/1 mL; SUS SCROFA PANCREAS 200 [kp_C]/1 mL; BOS TAURUS SPLEEN 200 [kp_C]/1 mL; SUS SCROFA SPLEEN 200 [kp_C]/1 mL
INACTIVE INGREDIENTS: ALCOHOL; WATER

Liver

Active Ingredients

Carduus Benedictus (30K), Carduus marianus (30K), Ceanothus americanus (6X), Chelidonium majus (30K), Chionanthus virginica (6X), Choline (30K), Coelliac plexus (8X, 200K), Duodenum (30K), Fumaric acid (30K), Gall bladder (30K), Inositol (30K), IL 4 (10X, 200K), Kalium sulfuricum (6X, 30K), Liver (6X, 200K), Lycopodium clavatum (30K), Natrium oxalaceticum (30K), Natrium pyruvicum (30K), Natrium sulphuricum (6X, 30K), Niacin (30K), Pancreas (8X, 200K), Spleen (6X, 200K), Taraxacum (30K), Vein (30K), Vitamin B1 (30K), Vitamin B12 (30K), Vitamin B2 (30K), Vitamin B6 (30K)

Purpose:

Carduus Benedictus | Drainage
Carduus marianus | Drainage
Ceanothus americanus | Spleen support
Chelidonium majus | Drainage
Chionanthus virginica | Drainage
Choline | Drainage
Coelliac plexus | Neurological support
Duodenum | Drainage
Fumaric acid | Cell respiration
Gall bladder | Regeneration
Inositol | Cell respiration
IL 4 | anti-inflammatory
Kalium sulfuricum | Drainage
Liver | Drainage
Lycopodium clavatum | Drainage
Natrium oxalaceticum | Cell respiration
Natrium pyruvicum | Cell respiration
Natrium sulphuricum | Drainage
Niacin | Anti-oxidant
Pancreas | Regeneration
Spleen | Regeneration
Taraxacum | Drainage
Vein | Circulatory support
Vitamin B1 | Nutritional Support
Vitamin B12 | Nutritional Support
Vitamin B2 | Nutritional Support
Vitamin B6 | Adrenal support

Uses

To help support the structure & function of the liver

Warnings

Stop use and ask a health care practitioner if symptoms persist for more than five days or worsen. If pregnant or breastfeeding, ask a health care practitioner before use.

Dosage

1-5 spray(s); 1-3 time(s) per day or as recommended by your health care practitioner.

KEEP OUT OF REACH OF CHILDREN

Keep this and all medicines out of reach of children.

Other Ingredients

20% Alcohol and 80% Water.

Other Information

Normal storage use.
Do not use if tamper-evident seal is broken or removed.

Questions

info@viatrexx.com

Principal Display Panel

ITEM: VPC0320
NDC 63776-300-15
Homeopathic remedy
Liver
• To help support the structure & function of the liver
Oral spray
50ml 1.7 oz
Viatrexx™ Bio Incorporated
Manufactured by Viatrexx
www.viatrexx.com
Newark, DE 19713

Liver
50 ml
1.7 oz
Viatrexx™ Bio Incorporated
ITEM: VPC0320
NDC: 63776-300-15
INDICATIONS:
To help support the structure & function of the liver.
DIRECTIONS:
1-5 spray(s); 1-3 time(s) per day or as recommended by your health care practitioner.
Mfg. for
Viatrexx Bio Incorporated.
www.viatrexx.com
Newark, DE 19713